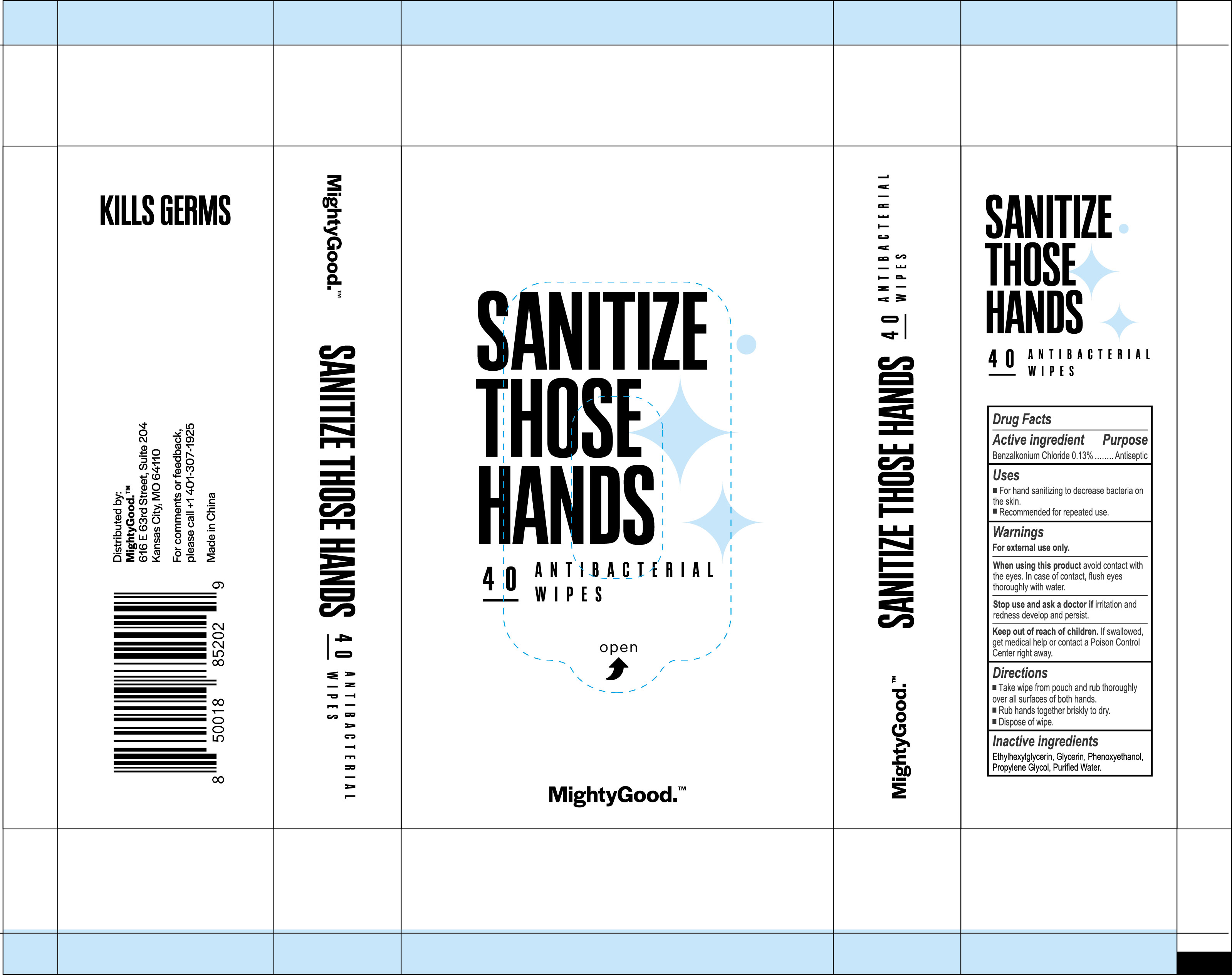 DRUG LABEL: SANITIZE THOSE HANDS 40PCS ANTIBACTERIAL WIPES
NDC: 79650-013 | Form: LIQUID
Manufacturer: Zhangzhou Zhongnan Nursing Products Co., Ltd.
Category: otc | Type: HUMAN OTC DRUG LABEL
Date: 20200828

ACTIVE INGREDIENTS: BENZALKONIUM CHLORIDE 0.13 mg/100 mL
INACTIVE INGREDIENTS: WATER; PHENOXYETHANOL; GLYCERIN; ETHYLHEXYLGLYCERIN; PROPYLENE GLYCOL

Active Ingredient

Benzalkonium Chloride 0.13%

Purpose

Antibacterial

Uses

To decrease bacteria on the skin that could cause disease

Warnings

For external use only.

When using this product avoid contact with the eyes. In case of contact , flush eyes thoroughly with water.

Stop use and ask a doctor if irritation and redness develop and persist.

Keep out of reach of children. If swallowed, get medical help or contact a Poison Control Center right away.

Directions

- Take wipe from pouch and rub thoroughly over all surfaces of both hands.
- Rub hands together briskly to dry.
- Dispose of wipe.

Other Information

- Keep containers tightly closed in a dry, cool and well-ventilated place.

Inactive Ingredients

Ethylhexylglycerin ,Glycerin,Phenoxyethanol, Propylene Glycol,Purified Water

Package Label/Principal Display Panel

NDC 79650--013-40; 170 mL